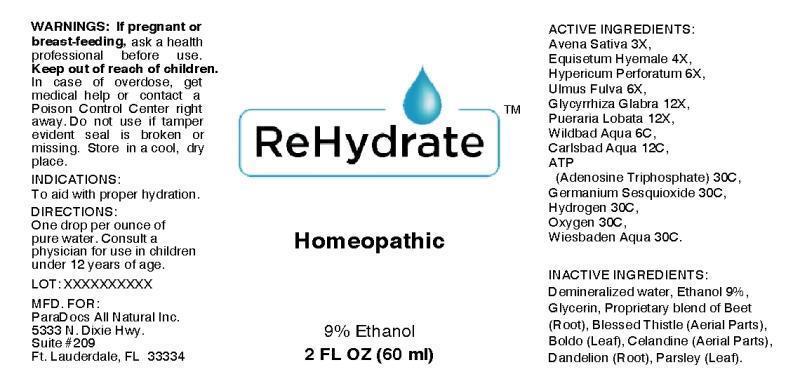 DRUG LABEL: REHYDRATE
NDC: 54638-0001 | Form: LIQUID
Manufacturer: ParaDocs All Natural Inc.
Category: homeopathic | Type: HUMAN OTC DRUG LABEL
Date: 20130807

ACTIVE INGREDIENTS: AVENA SATIVA FLOWERING TOP 3 [hp_X]/1 mL; EQUISETUM HYEMALE 4 [hp_X]/1 mL; HYPERICUM PERFORATUM 6 [hp_X]/1 mL; ULMUS RUBRA BARK 6 [hp_X]/1 mL; GLYCYRRHIZA GLABRA 12 [hp_X]/1 mL; PUERARIA MONTANA VAR. LOBATA WHOLE 12 [hp_X]/1 mL; WATER 6 [hp_C]/1 mL; ADENOSINE TRIPHOSPHATE 30 [hp_C]/1 mL; GERMANIUM SESQUIOXIDE 30 [hp_C]/1 mL; HYDROGEN 30 [hp_C]/1 mL; OXYGEN 30 [hp_C]/1 mL
INACTIVE INGREDIENTS: BETA VULGARIS; CENTAUREA BENEDICTA FLOWERING TOP; PEUMUS BOLDUS LEAF; CHELIDONIUM MAJUS FLOWERING TOP; TARAXACUM OFFICINALE ROOT; PETROSELINUM CRISPUM; ALCOHOL; GLYCERIN

DRUG FACTS:

ACTIVE INGREDIENTS:

Avena Sativa 3X, Equisetum Hyemale 4X, Hypericum Perforatum 6X, Ulmus Fulva 6X, Glycyrrhiza Glabra 12X, Pueraria Lobata 12X, Wildbad Aqua 6C, Carlsbad Aqua 12C, ATP (Adenosine Triphosphate) 30C, Germanium Sesquioxide 30C, Hydrogen 30C, Oxygen 30X, Wiesbaden Aqua 30C.

INDICATIONS:

To aid with proper hydration.

WARNINGS:

If pregnant or breast-feeding, ask a health professional before use.

Keep out of reach of children. In case of overdose, get medical help or contact a Poison Control Center right away.

Do not use if tamper evident seal is broken or missing.

STORAGE:

Store in a cool, dry place.

DIRECTIONS:

One drop per ounce of pure water. Consult a physician for use in children under 12 years of age.

INACTIVE INGREDIENTS:

Beet (Root), Blessed Thistle (Aerial Parts), Boldo (Leaf), Celandine (Aerial Parts), Dandelion (Root), Parsley (Leaf), Ethanol 9%, Glycerin 12%, Water

Keep out of reach of children. In case of overdose, get medical help or contact a Poison Control Center right away.

INDICATIONS:

To aid with proper hydration.

QUESTIONS:

MFD. FOR:

ParaDocs All Natural Inc.

5333 N. Dixie Hwy.

Suite #209

Ft. Lauderdale, FL 33334

PACKAGE DISPLAY LABEL:

ReHydrate

Homeopathic

2 FL OZ (60 ml)